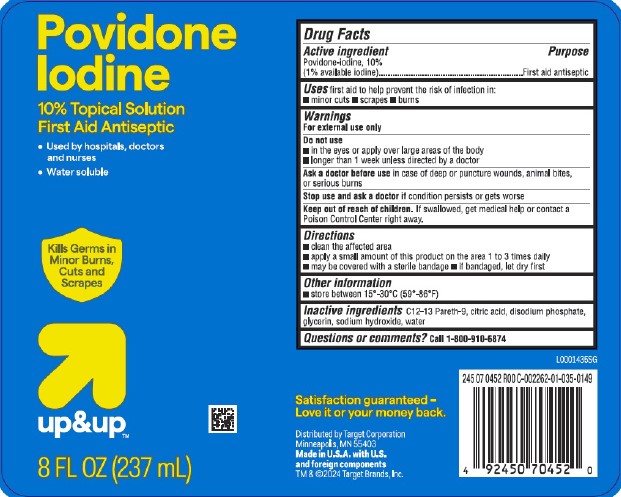 DRUG LABEL: First Aid Antiseptic
NDC: 11673-003 | Form: SOLUTION
Manufacturer: Target Corporation
Category: otc | Type: HUMAN OTC DRUG LABEL
Date: 20260218

ACTIVE INGREDIENTS: POVIDONE-IODINE 10 mg/1 mL
INACTIVE INGREDIENTS: C12-13 PARETH-9; CITRIC ACID MONOHYDRATE; SODIUM PHOSPHATE, DIBASIC, ANHYDROUS; GLYCERIN; SODIUM HYDROXIDE; WATER

Up & Up 050.002/050AE
Povidone-Iodine Solution, 10%

Active ingredient

Povidone-Iodine, 10% (1% available iodine)

Purpose

First aid antiseptic

Uses

first aid to help prevent the risk of infection in:

- minor cuts
- scrapes
- burns

Warnings

For external use only

Do not use

- in the eyes or apply over larger areas of the body
- longer than 1 week unless directed by a doctor

Ask a doctor before use

in case of deep or puncture wounds, animal bites or serious burn

Stop use and ask a doctor if

- condition persists or gets worse

Keep out of reach of children

If swallowed, get medical help or contact a Poison Control Center right away.

Directions

- clean the affected area
- apply a small amount of this product on the area 1 to 3 times daily
- may be covered with a sterile bandage
- If bandaged, let dry first

Other information

- store between 15º-30ºC (59º-86ºF)

Inactive ingredients

C12-13 Pareth-9, citric acid, disodium phosphate, glycerin, sodium hydroxide, water

Questions or comments?

Call 1-800-910-6874

Adverse reaction

Satisfaction guaranteed - Love it or your money back.

Distributed by Target Corporation

Minneapolis, MN 55403

Made in U.S.A. with U.S. and foreign components

TM & 2024 Target Brands, Inc.

principal display panel

Povidone Iodine

10% Topical Solution

First Aid Antiseptic

- Used by hospitals, doctors and nurses
- Water soluble

Kills Germs in Minor Burns, Cuts and Scrapes

up & up™

8 FL OZ (237 mL)